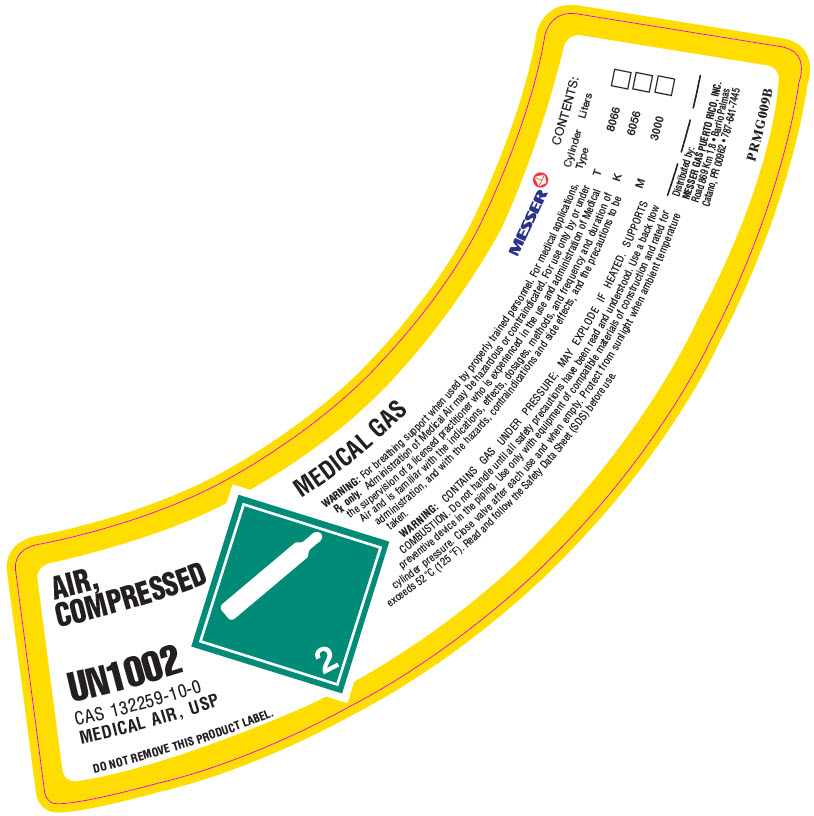 DRUG LABEL: Air, Compressed
NDC: 52374-006 | Form: GAS
Manufacturer: Messer Gas Puerto Rico Inc
Category: prescription | Type: HUMAN PRESCRIPTION DRUG LABEL
Date: 20251118

ACTIVE INGREDIENTS: OXYGEN 21 L/100 L
INACTIVE INGREDIENTS: NITROGEN 79 L/100 L

Messer PR - AIR, COMPRESSED

WARNINGS AND PRECAUTIONS SECTION

WARNING:For breathing support when used by properly trained personnel. For medical applications, Rx only.Administration of Medical Air may be hazardous or contraindicated. For use only by or under the supervision of a licensed practitioner who is experienced in the use and administration of Medical Air and is familiar with the indications, effects, dosages, methods, and frequency and duration of administration, and with the hazards, contraindications and side effects, and the precautions to be taken.
WARNING:CONTAINS GAS UNDER PRESSURE; MAY EXPLODE IF HEATED. SUPPORTS COMBUSTION. Do not handle until all safety precautions have been read and understood. Use a back flow preventive device in the piping. Use only with equipment of compatible materials of construction and rated for cylinder pressure. Close valve after each use and when empty. Protect from sunlight when ambient temperature exceeds 52°C (125°F). Read and follow the Safety Data Sheet (SDS) before use.

Un-Coded Section

CONTENTS:
Cylinder Type | Liters
T | 8066 | [_]
K | 6056 | [_]
M | 3000 | [_]
______ | ______ | ______

Distributed by:
Messer Gas Puerto Rico Inc,
Road 869 Km 1.8,
Barrio Palmas, Catano PR 00962
(787-641-7445)
PRMG009B

PACKAGE LABEL.PRINCIPAL DISPLAY PANEL

Messer
AIR, COMPRESSED USP
UN1002
CAS 7727-37-9
MEDICAL AIR
DO NOT REMOVE THIS PRODUCT LABEL.
MEDICAL GAS